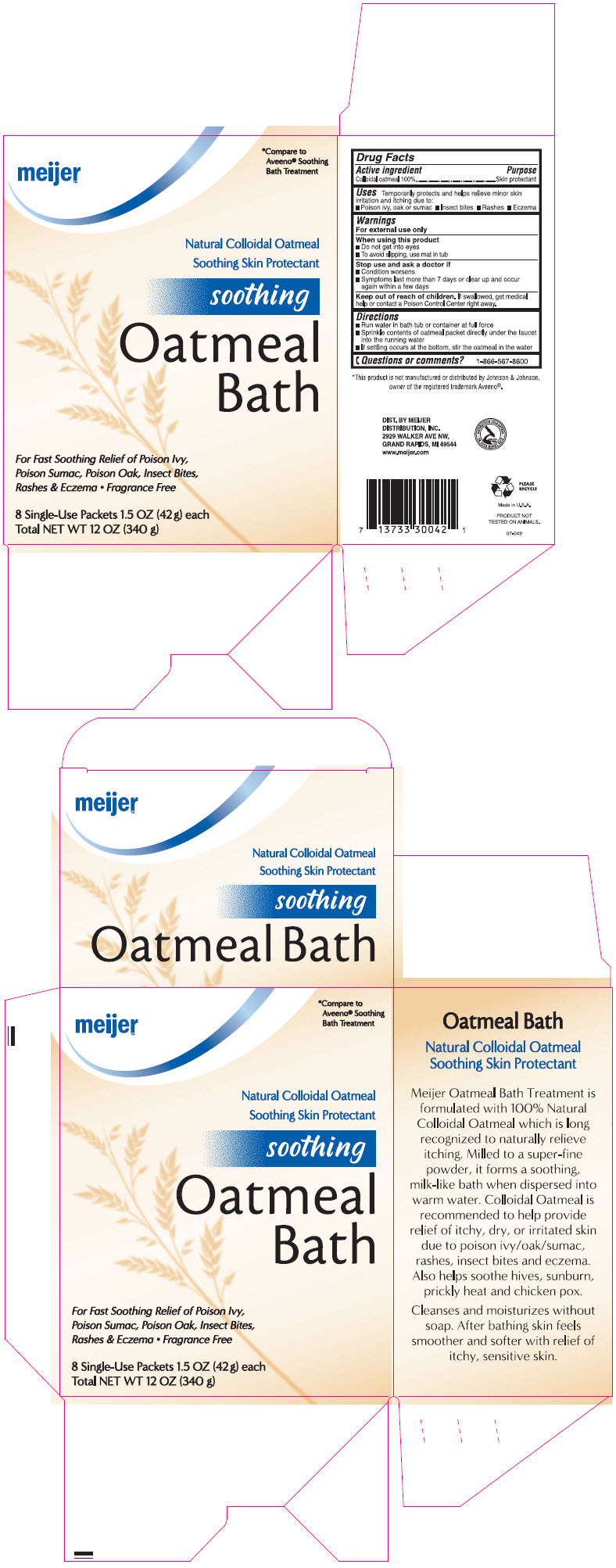 DRUG LABEL: Meijer Oatmeal Bath 
NDC: 41250-642 | Form: POWDER, FOR SOLUTION
Manufacturer: Meijer Distribution, INC
Category: otc | Type: HUMAN OTC DRUG LABEL
Date: 20220124

ACTIVE INGREDIENTS: Oatmeal 1000 mg/1 g

Meijer™ Oatmeal Bath
Skin Protectant

Drug Facts

Active ingredient

Colloidal Oatmeal 100%

Purpose

Skin Protectant

Uses

Temporarily protects and helps relieve minor skin irritation and itching due to:

♦ Poison Ivy, oak or sumac
♦ Insect bites
♦ Rashes
♦ Eczema

Warnings

For external use only

When using this product

♦ Do not get into eyes
♦ To avoid slipping, use mat in tub

Stop use and ask a doctor if

♦ Condition worsens
♦ Symptoms last more than 7 days or clear up and occur again within a few days

Keep out of reach of children. If swallowed, get medical help or contact a Poison Control Center right away.

Directions

♦ Run water in bath tub or container at full force
♦ Sprinkle contents of oatmeal packet directly under the faucet into the running water
♦ If settling occurs at the bottom, stir the oatmeal in the water

Questions or comments?

1-866-567-8600

DIST. BY MEIJER
DISTRIBUTION, INC.
2929 WALKER AVE NW,
GRAND RAPIDS, MI 49544

PRINCIPAL DISPLAY PANEL - 42 g Packet Carton

meijer™

*Compare to
Aveeno® Soothing
Bath Treatment

Natural Colloidal Oatmeal
Soothing Skin Protectant

soothing

Oatmeal
Bath

For Fast Soothing Relief of Poison Ivy,
Poison Sumac, Poison Oak, Insect Bites,
Rashes & Eczema • Fragrance Free

8 Single-Use Packets 1.5 OZ (42 g) each
Total NET WT 12 OZ (340 g)